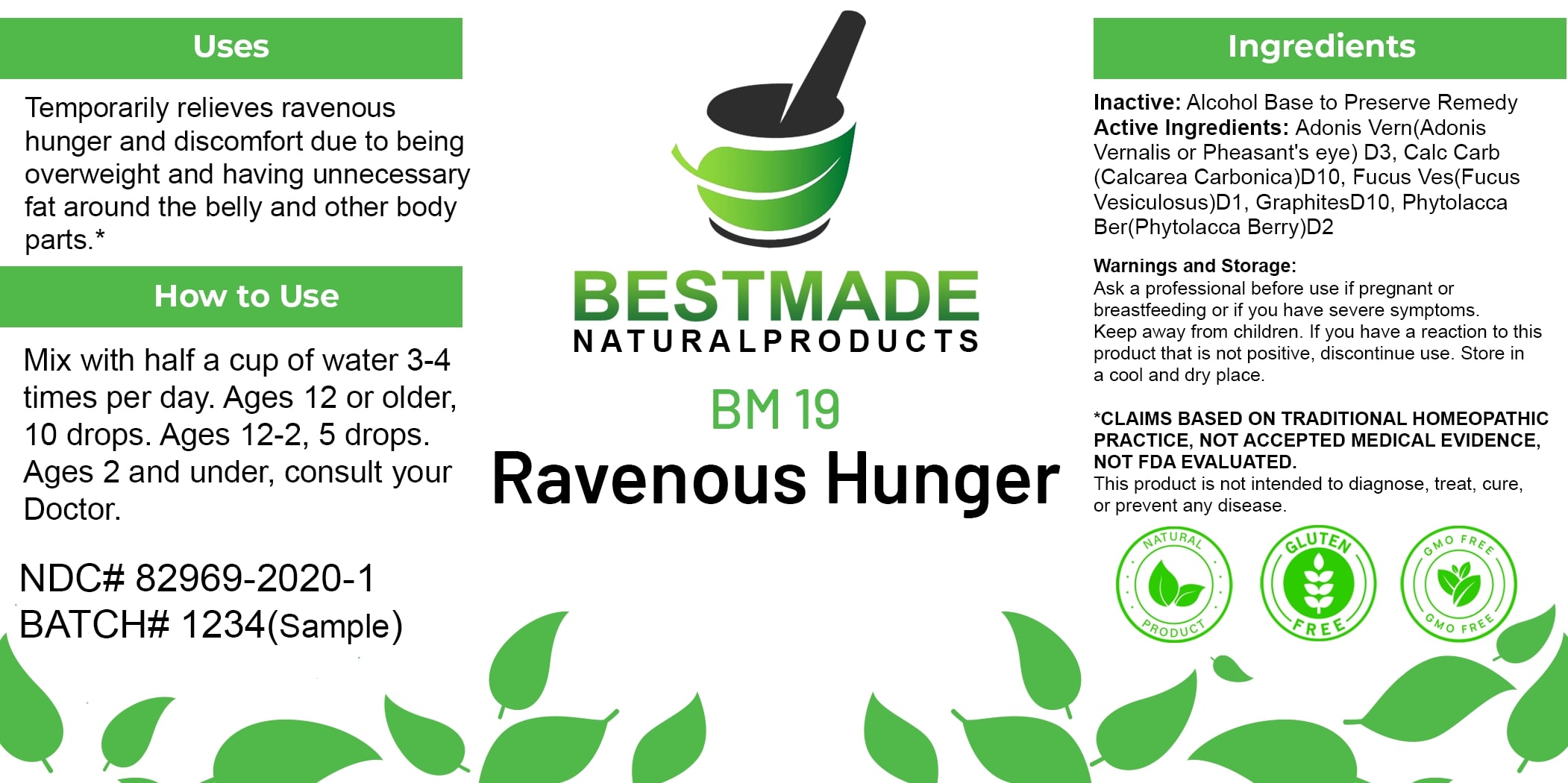 DRUG LABEL: Bestmade Natural Products BM19
NDC: 82969-2019 | Form: LIQUID
Manufacturer: Bestmade Natural Products
Category: homeopathic | Type: HUMAN OTC DRUG LABEL
Date: 20250122

ACTIVE INGREDIENTS: ADONIS VERNALIS 30 [hp_C]/30 [hp_C]; GRAPHITE 30 [hp_C]/30 [hp_C]; PHYTOLACCA AMERICANA ROOT 30 [hp_C]/30 [hp_C]; OYSTER SHELL CALCIUM CARBONATE, CRUDE 30 [hp_C]/30 [hp_C]; FUCUS VESICULOSUS 30 [hp_C]/30 [hp_C]
INACTIVE INGREDIENTS: ALCOHOL 30 [hp_C]/30 [hp_C]

BM19

DOSAGE AND ADMINISTRATION

How to Use
Mix with half a cup of water 3-4 times per day. Ages 12 or older, 10 drops. Ages 12-2, 5 drops. Ages 2 and under, consult your Doctor.

INACTIVE INGREDIENT

Ingredients
Inactive: Alcohol Base to Preserve Remedy

Uses
Temporarily relieves ravenous hunger and discomfort due to being overweight and having unnecessary fat around the belly and other body parts.*

*CLAIMS BASED ON TRADITIONAL HOMEOPATHIC PRACTICE, NOT ACCEPTED MEDICAL EVIDENCE, NOT FDA EVALUATED.
This product is not intended to diagnose, treat, cure, or prevent any disease.

Active Ingredients:

Adonis Vern (Adonis Vernalis or Pheasant’s eye) D3, Calc Carb (Calcarea Carbonica) D10, Fucus Ves (Fucus Vesiculosus) D1, Graphites D10, Phytolacca Ber (Phytolacca Berry) D2

KEEP OUT OF REACH OF CHILDREN

Warnings and Storage:
Ask a professional before use if pregnant or breastfeeding or if you have severe symptoms. Keep away from children. If you have a reaction to this product that is not positive, discontinue use. Store in a cool and dry place.

Uses
Temporarily relieves ravenous hunger and discomfort due to being overweight and having unnecessary fat around the belly and other body parts.*

*CLAIMS BASED ON TRADITIONAL HOMEOPATHIC PRACTICE, NOT ACCEPTED MEDICAL EVIDENCE, NOT FDA EVALUATED.
This product is not intended to diagnose, treat, cure, or prevent any disease.

Warnings and Storage:
Ask a professional before use if pregnant or breastfeeding or if you have severe symptoms. Keep away from children. If you have a reaction to this product that is not positive, discontinue use. Store in a cool and dry place.

*CLAIMS BASED ON TRADITIONAL HOMEOPATHIC PRACTICE, NOT ACCEPTED MEDICAL EVIDENCE, NOT FDA EVALUATED.
This product is not intended to diagnose, treat, cure, or prevent any disease.

Entire package label